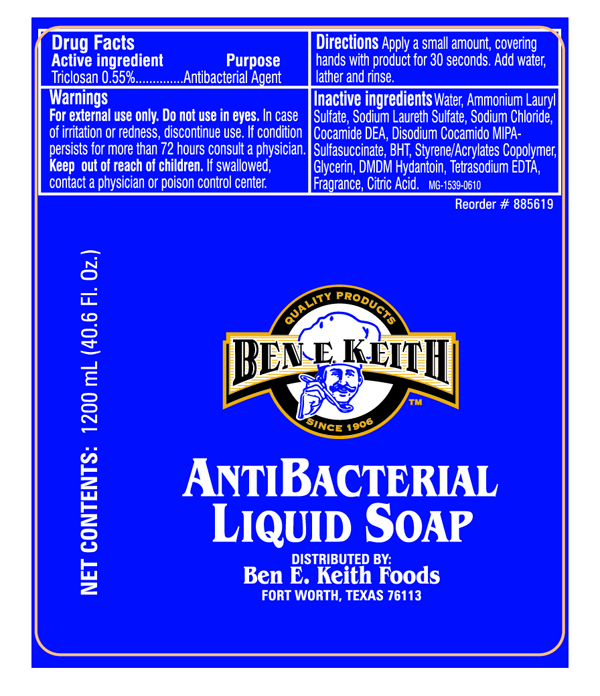 DRUG LABEL: Ben E. Keith
NDC: 50980-078 | Form: LIQUID
Manufacturer: Ben E. Keith Foods
Category: otc | Type: HUMAN OTC DRUG LABEL
Date: 20100618

ACTIVE INGREDIENTS: Triclosan 0.5 mL/100 mL

Drug Facts

ACTIVE INGREDIENT

Triclosan 0.55 %

WARNINGS

For external use only. Do not use in eyes.

ASK DOCTOR

In rare instances of irritation or redness, discontinue use if irritation or redness develop. If condition persists for more than 72 hours consult a physician. If swallowed, contact a physician or poison control center. Keep out of reach of children.

INDICATIONS AND USAGE

For handwashing to decrease bacteria on skin.

WHEN USING

Apply a small amount, covering hands with product for 30 seconds. Add water, lather and rinse.

INACTIVE INGREDIENT

Water, Ammonium Lauryl Sulfate, Sodium Laureth Sulfate, Sodium Chloride, Cocamide DEA, Disodium Cocamido MIPA-Sulfosuccinate, BHT, Styrene/Acrylates Copolymer, Glycerin, DMDM Hydantoin, Tetrasodium EDTA, Fragrance, Citric Acid.

Ben E. Keith 1200 mL bottle label